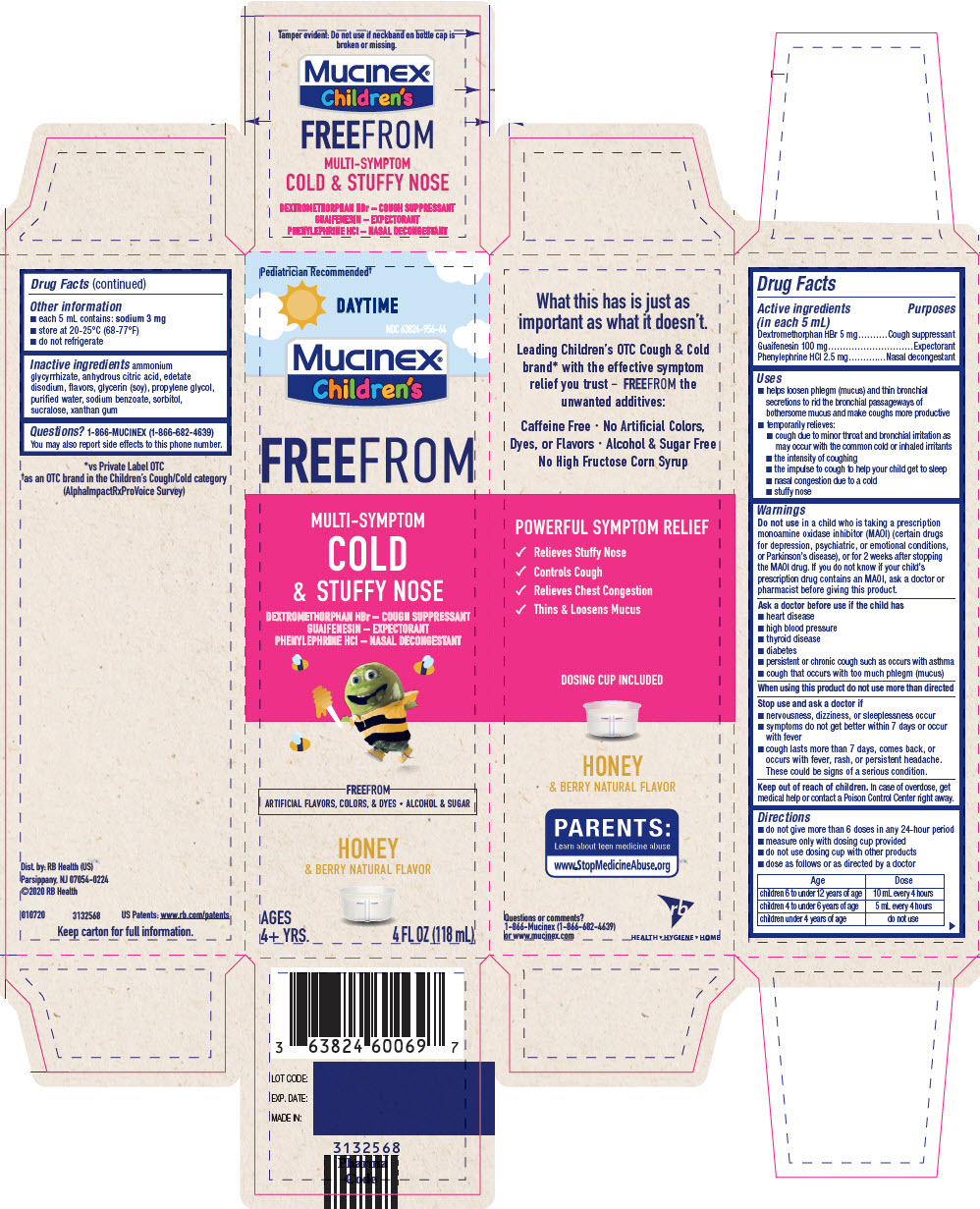 DRUG LABEL: Mucinex Childrens FreeFrom Multi-Symptom Cold and Stuffy Nose
NDC: 63824-956 | Form: SOLUTION
Manufacturer: RB Health (US) LLC
Category: otc | Type: HUMAN OTC DRUG LABEL
Date: 20241219

ACTIVE INGREDIENTS: DEXTROMETHORPHAN HYDROBROMIDE 5 mg/5 mL; GUAIFENESIN 100 mg/5 mL; PHENYLEPHRINE HYDROCHLORIDE 2.5 mg/5 mL
INACTIVE INGREDIENTS: AMMONIUM GLYCYRRHIZATE; ANHYDROUS CITRIC ACID; EDETATE DISODIUM; PROPYLENE GLYCOL; WATER; SODIUM BENZOATE; SORBITOL; SUCRALOSE; XANTHAN GUM

Mucinex® Children's FreeFrom Multi-Symptom Cold & Stuffy Nose

Drug Facts

ACTIVE INGREDIENT

PURPOSE

Active ingredients (in each 5 mL) | Purposes
Dextromethorphan HBr 5 mg | Cough suppressant
Guaifenesin 100 mg | Expectorant
Phenylephrine HCl 2.5 mg | Nasal decongestant

Uses

- helps loosen phlegm (mucus) and thin bronchial secretions to rid the bronchial passageways of bothersome mucus and make coughs more productive
- temporarily relieves:
  - cough due to minor throat and bronchial irritation as may occur with the common cold or inhaled irritants
  - the intensity of coughing
  - the impulse to cough to help your child get to sleep
  - nasal congestion due to a cold
  - stuffy nose

Warnings

DO NOT USE

Do not usein a child who is taking a prescription monoamine oxidase inhibitor (MAOI) (certain drugs for depression, psychiatric, or emotional conditions, or Parkinson's disease), or for 2 weeks after stopping the MAOI drug. If you do not know if your child's prescription drug contains an MAOI, ask a doctor or pharmacist before giving this product.

Ask a doctor before use if the child has

- heart disease
- high blood pressure
- thyroid disease
- diabetes
- persistent or chronic cough such as occurs with asthma
- cough that occurs with too much phlegm (mucus)

When using this product do not use more than directed

Stop use and ask a doctor if

- nervousness, dizziness, or sleeplessness occur
- symptoms do not get better within 7 days or occur with fever
- cough lasts more than 7 days, comes back, or occurs with fever, rash, or persistent headache. These could be signs of a serious condition.

Keep out of reach of children.In case of overdose, get medical help or contact a Poison Control Center right away.

Directions

- do not give more than 6 doses in any 24-hour period
- measure only with dosing cup provided
- do not use dosing cup with other products
- dose as follows or as directed by a doctor

Age | Dose
children 6 to under 12 years of age | 10 mL every 4 hours
children 4 to under 6 years of age | 5 mL every 4 hours
children under 4 years of age | do not use

Other information

- each 5 mL contains: sodium 3 mg
- store at 20-25°C (68-77°F)
- do not refrigerate

Inactive ingredients

ammonium glycyrrhizate, anhydrous citric acid, edetate disodium, flavors, glycerin (soy), propylene glycol, purified water, sodium benzoate, sorbitol, sucralose, xanthan gum

Questions?

1-866-MUCINEX (1-866-682-4639)
You may also report side effects to this phone number.

Dist. by: RB Health (US)
Parsippany, NJ 07054-0224

PRINCIPAL DISPLAY PANEL - 118 mL Bottle Carton

Pediatrician Recommended†

DAYTIME

NDC 63824-956-64

Mucinex®
Children's

FREEFROM

MULTI-SYMPTOM
COLD
& STUFFY NOSE

DEXTROMETHORPHAN HBr – COUGH SUPPRESSANT
GUAIFENESIN – EXPECTORANT
PHENYLEPHRINE HCl – NASAL DECONGESTANT

FREEFROM
ARTIFICIAL FLAVORS, COLORS, & DYES • ALCOHOL & SUGAR

HONEY
& BERRY NATURAL FLAVOR

AGES
4+ YRS.

4 FL OZ (118 mL)